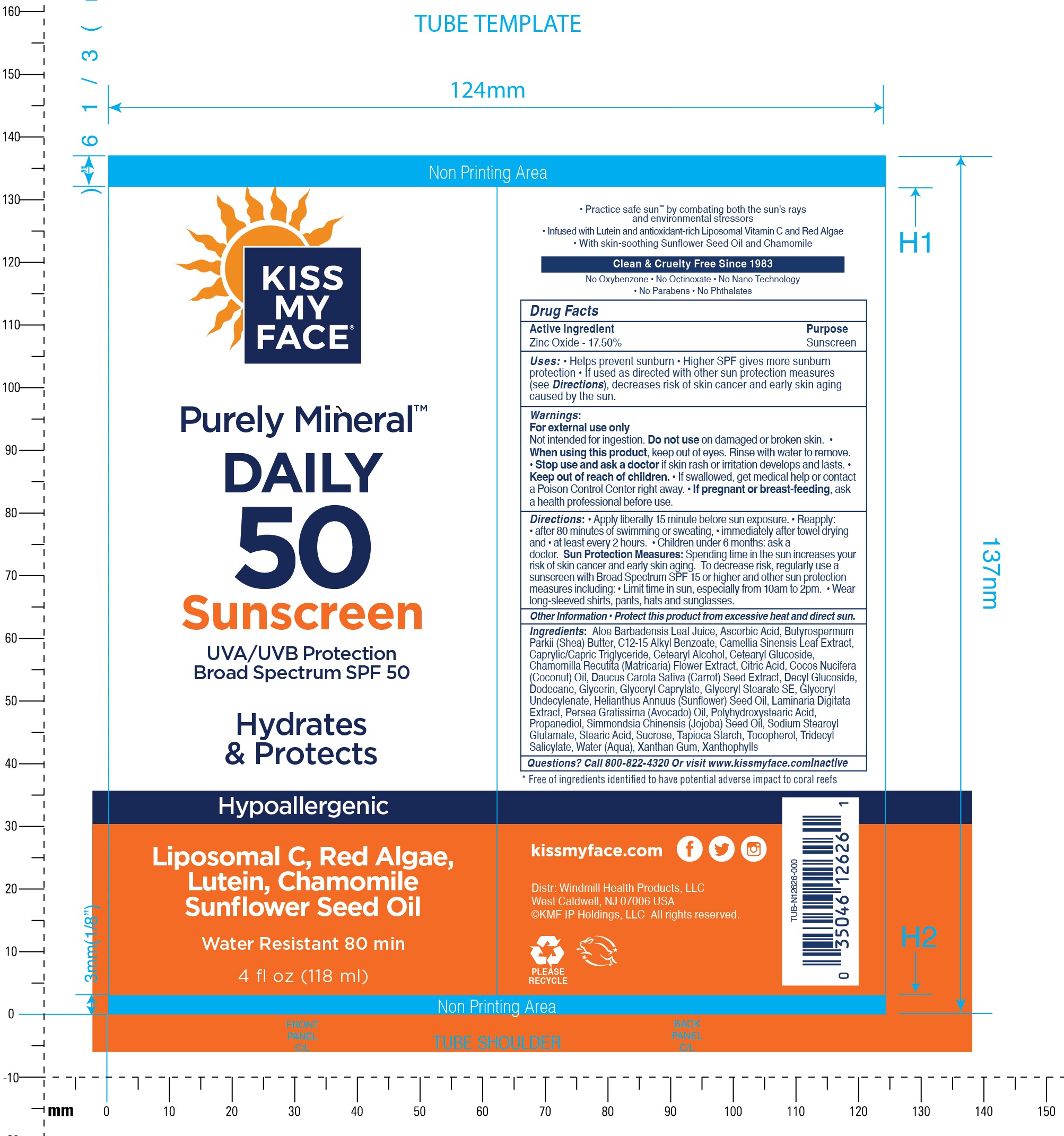 DRUG LABEL: Kiss My Face Purely Mineral Daily 50 Sunscreen SPF 50
NDC: 74154-903 | Form: LOTION
Manufacturer: Windmill Health Products, LLC
Category: otc | Type: HUMAN OTC DRUG LABEL
Date: 20260225

ACTIVE INGREDIENTS: ZINC OXIDE 175 mg/1 mL
INACTIVE INGREDIENTS: SUCROSE; TRIDECYL SALICYLATE; WATER; XANTHAN GUM; ALOE VERA LEAF JUICE; ASCORBIC ACID; MEDIUM-CHAIN TRIGLYCERIDES; CETOSTEARYL ALCOHOL; CETEARYL GLUCOSIDE; CITRIC ACID MONOHYDRATE; COCONUT; DAUCUS CAROTA SUBSP. SATIVUS SEED; DECYL GLUCOSIDE; DODECANE; GLYCERIN; GLYCERYL MONOCAPRYLATE; GLYCERYL STEARATE SE; HELIANTHUS ANNUUS FLOWERING TOP; LAMINARIA DIGITATA; AVOCADO; PROPANEDIOL; SODIUM STEAROYL GLUTAMATE; STEARIC ACID

Kiss My Face Purely Mineral Daily 50 Sunscreen SPF 50

Active Ingredient

Zinc Oxide - 17.50%

Purpose

Sunscreen

Uses:

- Helps prevent sunburn
- Higher SPF gives more sunburn protection
- If used as directed with other sun protection measures (see Directions), decreases risk of skin cancer and early skin aging caused by the sun.

Warnings:

For external use only
Not intended for ingestion.

Do not use

on damaged or broken skin.

When using this product,

keep out of eyes. Rinse with water to remove.

Stop use and ask a doctor

- if skin rash or irritation develops and lasts.

Keep out of reach of children.

- If swallowed, get medical help or contact a Poison Control Center right away.

If pregnant or breast-feeding,

ask a health professional before use.

Directions:

- Apply liberally 15 minute before sun exposure.
- Reapply:
- after 80 minutes of swimming or sweating,
- immediately after towel drying and at least every 2 hours.
- Children under 6 months: ask a doctor. Sun Protection Measures:Spending time in the sun increases your risk of skin cancer and early skin aging. To decrease risk, regularly use a sunscreen with Broad Spectrum SPF 15 or higher and other sun protection measures including:
- Limit time in sun, especially from 10am to 2pm.
- Wear long-sleeved shirts, pants, hats and sunglasses.

Other Information

- Protect this product from excessive heat and direct sun.

Ingredients:

Aloe Barbadensis Leaf Juice, Ascorbic Acid, Butyrospermum Parkii (Shea) Butter, C12-15 Alkyl Benzoate, Camellia Sinensis Leaf Extract, Caprylic/Capric Triglyceride, Cetearyl Alcohol, Cetearyl Glucoside, Chamomilla Recutlta (Matricaria) Flower Extract, Citric Acid, Cocos Nucifera (Coconut) Oil, Daucus Carota Sativa (Carrot) Seed Extract, Decyl Glucoside, Dodecane, Glycerin, Glyceryl Caprylate, Glyceryl Stearate SE, Glyceryl Undecylenate, Helianthus Annuus (Sunflower) Seed Oil, Laminaria Digitata Extract, Persea Gratissima (Avocado) Oil, Polyhydroxvstearic Acid, Propanediol, Simmondsia Chinensis (Jojoba) Seed Oil, Sodium Stearoyl Glutamate, Stearic Acid, Sucrose, Tapioca Starch, Tocopherol, Tridecyl Salicylate, Water (Aqua), Xanthan Gum, Xanthophylls

Questions?

Call 800-822-4320 Or visit www.kissmyface.comlnactive